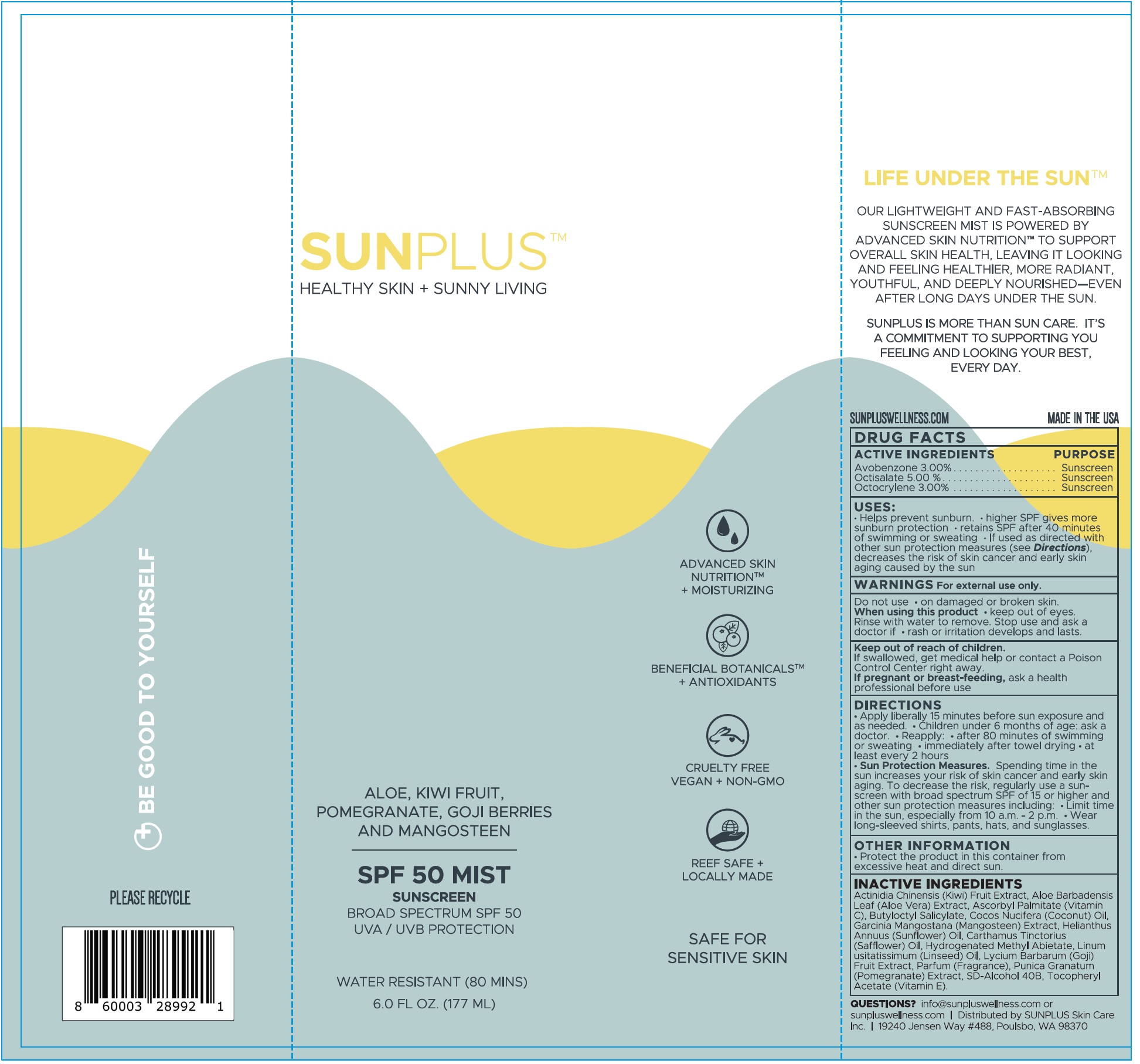 DRUG LABEL: Sunplus Mist Sunscreen SPF 50
NDC: 84661-894 | Form: LIQUID
Manufacturer: SUNPLUS SKIN CARE LLC
Category: otc | Type: HUMAN OTC DRUG LABEL
Date: 20251013

ACTIVE INGREDIENTS: AVOBENZONE 30 mg/1 mL; OCTISALATE 50 mg/1 mL; OCTOCRYLENE 30 mg/1 mL
INACTIVE INGREDIENTS: KIWI FRUIT; ALOE VERA LEAF; ASCORBYL PALMITATE; BUTYLOCTYL SALICYLATE; COCONUT OIL; HELIANTHUS ANNUUS FLOWERING TOP; SAFFLOWER; HYDROGENATED METHYL ABIETATE; FLAX SEED; LYCIUM BARBARUM FRUIT; PUNICA GRANATUM ROOT BARK; .ALPHA.-TOCOPHEROL ACETATE

Sunplus Mist Sunscreen SPF 50

ACTIVE INGREDIENTS

Avobenzone 3.00%
Octisalate 5.00%
Octocrylene 3.00%

PURPOSE

Sunscreen

USES:

• Helps prevent sunburn. • higher SPF gives more sunburn protection. • retains SPF after 40 minutes of swimming or sweating • If used as directed with other sun protection measures (see Directions), decreases the risk of skin cancer and early skin aging caused by the sun

WARNINGS

For external use only.

Do not use

on damaged or broken skin.

When using this product

keep out of eyes. Rinse with water to remove.

Stop use and ask a doctor

- if rash or irritation develops and lasts.

Keep out of reach of children.

If swallowed, get medical help or contact a Poison Control Center right away.

If pregnant or breast-feeding,

ask a health professional before use

DIRECTIONS

Apply liberally 15 minutes before sun exposure and as needed. • Children under 6 months of age: ask a doctor. • Reapply: after 80 minutes of swimming or sweating. • immediately after towel drying. • at least every 2 hours

• Sun Protection Measures:Spending time in the sun increases your risk of skin cancer and early skin aging. To decrease the risk, regularly use a sunscreen with a broad spectrum SPF of 15 or higher and other sun protection measures including: • Limit time in the sun, especially from 10 a.m - 2 p.m. • Wear long-sleeved shirts, pants, hats, and sunglasses.

OTHER INFORMATION

- Protect the product in this container from excessive heat and direct sun.

INACTIVE INGREDIENTS

Actinidia Chinensis (Kiwi) Fruit Extract, Aloe barbadensis Leaf (Aloe Vera) Extract, Ascorbyl Palmitate (Vitamin C), Butyloctyl Salicylate, Cocos Nucifera (Coconut) Oil, Garcinia Mangostana (Mangosteen) Extract, Helianthus Annuus (Sunflower) Oil, Carthamus Tinctarius (Safflower) Oil, Hydrogenated Methyl Abietate, Linum usitatissimum (Linseed) Oil, Lycium Barbarum (Goji) Fruit Extract, Parfum (Fragrance), Punica Granatum (Pomegranate) Extract, SD-Alcohol 40B, Tocopheryl Acetate (Vitamin E).

QUESTIONS?

info@sunpluswellness.com or sunpluswellness.com